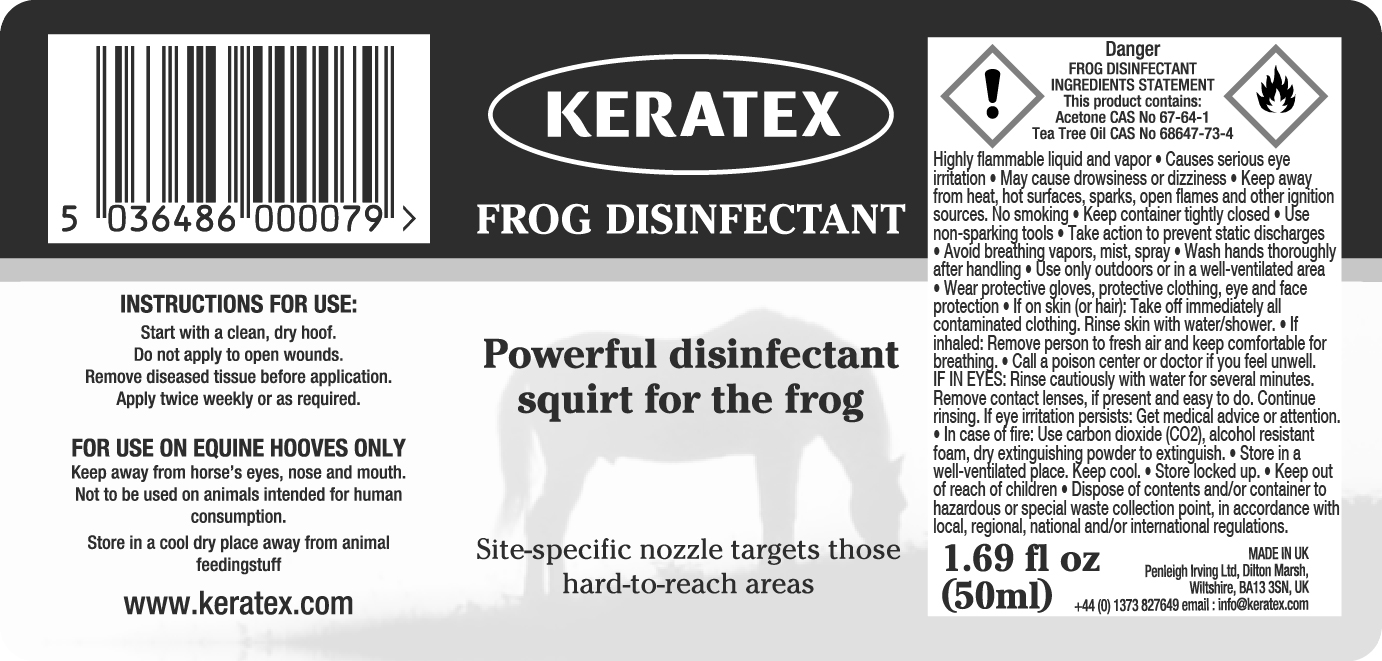 DRUG LABEL: Keratex
NDC: 27426-081 | Form: LIQUID
Manufacturer: Penleigh Irving Ltd
Category: animal | Type: OTC ANIMAL DRUG LABEL
Date: 20250530

ACTIVE INGREDIENTS: ACETONE 99 mg/100 mL; TEA TREE OIL 1 mg/100 mL

SAFE HANDLING WARNING

Highly flammable liquid and vapor. Causes serious eye irritation. May cause drowsiness or dizziness. Keep away from heat, hot surfaces, sparks, open flames and other ignition sources. No smoking. Keep container tightly closed. Use non-sparking tools. Take action to prevent static discharges. Avoid breathing vapors, mist, spray. Wash hands thoroughly after handling. Use only outdoors or in a well-ventilated area. Wear protective gloves, protective clothing, eye and face protection. If on skin (or hair): Take off immediately all contaminated clothing. Rinse skin with water/shower. If inhaled: Remove person to fresh air and keep comfortable for breathing. Call a poison center or doctor if you feel unwell. IF IN EYES: Rinse cautiously with water for several minutes. Remove contact lenses, if present and easy to do. Continue rinsing. If eye irritation persists: Get medical advice or attention. In case of fire: Use carbon dioxide (CO2), alcohol resistant foam, dry extinguishing powder to extinguish. Store in a well-ventilated place. Keep cool. Store locked up. Keep out of reach of children. Dispose of contents and/or container to hazardous or special waste collection point, in accordance with local, regional, national and/or international regulations.

PACKAGE LABEL

Keratex Frog Disinfectant

Powerful disinfectant squirt for the frog

Site-specific nozzle targets those hard-to-reach areas

Instructions for use: Start with a clean, dry hoof. Do not apply to open wounds. Remove diseased tissue before application. Apply twice weekly or as required.

Frog Disinfectant Ingredients Statement: Acetone CAS No. 67-64-1. Tea Tree Oil CAS No. 686-47-73-4.

For use on equine hooves only. Keep away from horse's eyes, nose and mouth. Not to be used on animals intended for human consumption. Store in a cool dry place away from animal feedingstuff.

1.69 fl oz (50ml)

MADE IN UK

Penleigh Irving Ltd.

Dilton Marsh, Wiltshire, BK13 3SN, UK

+44 (0) 1373 827649 email: info@keratex.com

www.keratex.com